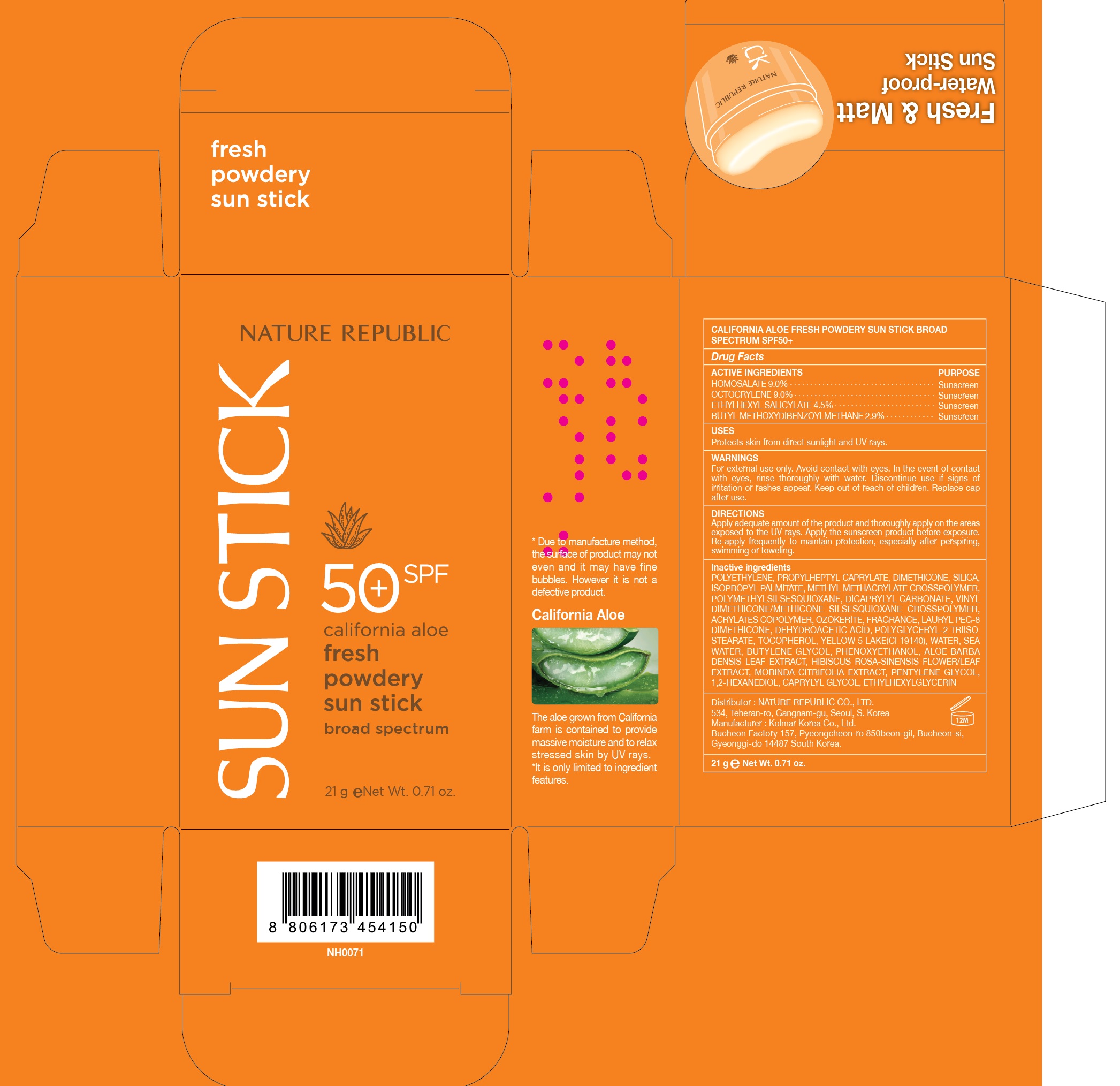 DRUG LABEL: CALIFORNIA ALOE FRESH POW DERY SUN
NDC: 51346-532 | Form: STICK
Manufacturer: NATURE REPUBLIC CO., LTD.
Category: otc | Type: HUMAN OTC DRUG LABEL
Date: 20260113

ACTIVE INGREDIENTS: HOMOSALATE 1.89 g/21 g; OCTOCRYLENE 1.89 g/21 g; OCTISALATE 0.94 g/21 g; AVOBENZONE 0.6 g/21 g
INACTIVE INGREDIENTS: PROPYLHEPTYL CAPRYLATE; DIMETHICONE

California Aloe Fresh Powdery Sun Stick SPF 50

Active Ingredients

HOMOSALATE 9.0%
OCTOCRYLENE 9.0%
ETHYLHEXYL SALICYLATE 4.5%
BUTYL METHOXYDIBENZOYLMETHANE 2.9%

Purpose

Sunscreen

Uses

Protects skin from direct sunlight and UV rays.

WARNINGS

For external use only. Avoid contact with eyes. In the event of contact with eyes, rinse thoroughly with water. Discontinue use if signs of irritation or rashes appear. Keep out of reach of children. Replace cap after use.

Keep out of reach of children.

Directions

Apply adequate amount of the product and thoroughly apply on the areas exposed to the UV rays. Apply the sunscreen product before exposure. Re-apply frequently to maintain protection, especially after perspiring, swimming or toweling.

Inactive Ingredients

POLYETHYLENE, PROPYLHEPTYL CAPRYLATE, DIMETHICONE, SILICA, ISOPROPYL PALMITATE, METHYL METHACRYLATE CROSSPOLYMER, POLYMETHYLSILSESQUIOXANE, DICAPRYLYL CARBONATE, VINYL DIMETHICONE/METHICONE SILSESQUIOXANE CROSSPOLYMER, ACRYLATES COPOLYMER, OZOKERITE, FRAGRANCE, LAURYL PEG-8 DIMETHICONE, DEHYDROACETIC ACID, POLYGLYCERYL-2 TRIISOSTEARATE, TOCOPHEROL, YELLOW 5 LAKE(CI 19140), WATER, SEA WATER, BUTYLENE GLYCOL, PHENOXYETHANOL, ALOE BARBADENSIS LEAF EXTRACT, HIBISCUS ROSA-SINENSIS FLOWER/LEAF EXTRACT, MORINDA CITRIFOLIA EXTRACT, PENTYLENE GLYCOL, 1,2-HEXANEDIOL, CAPRYLYL GLYCOL, ETHYLHEXYLGLYCERIN, LINALOOL, LIMONENE